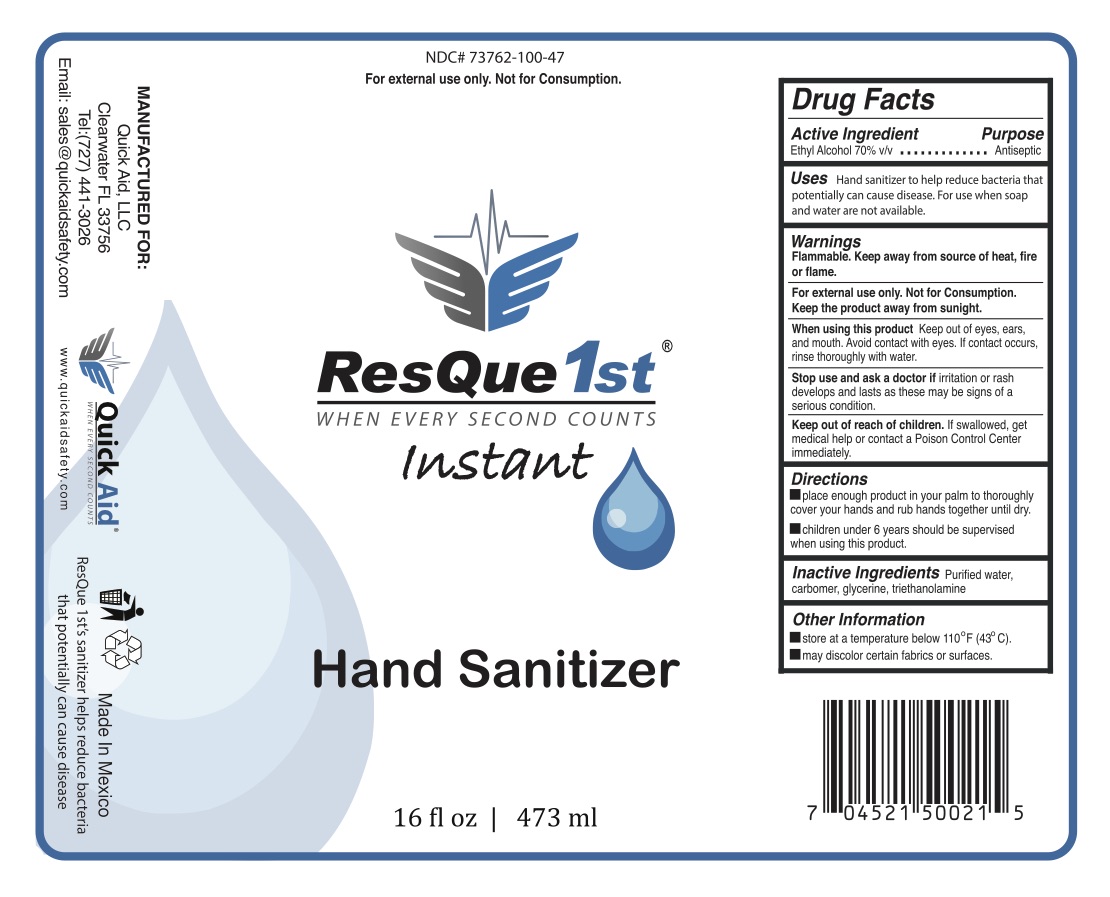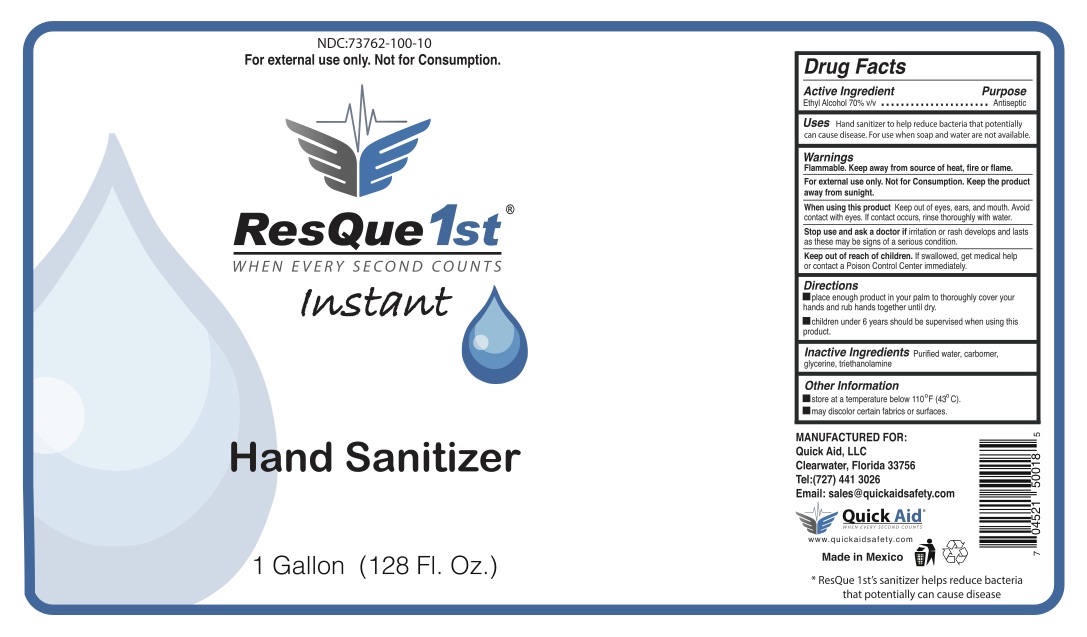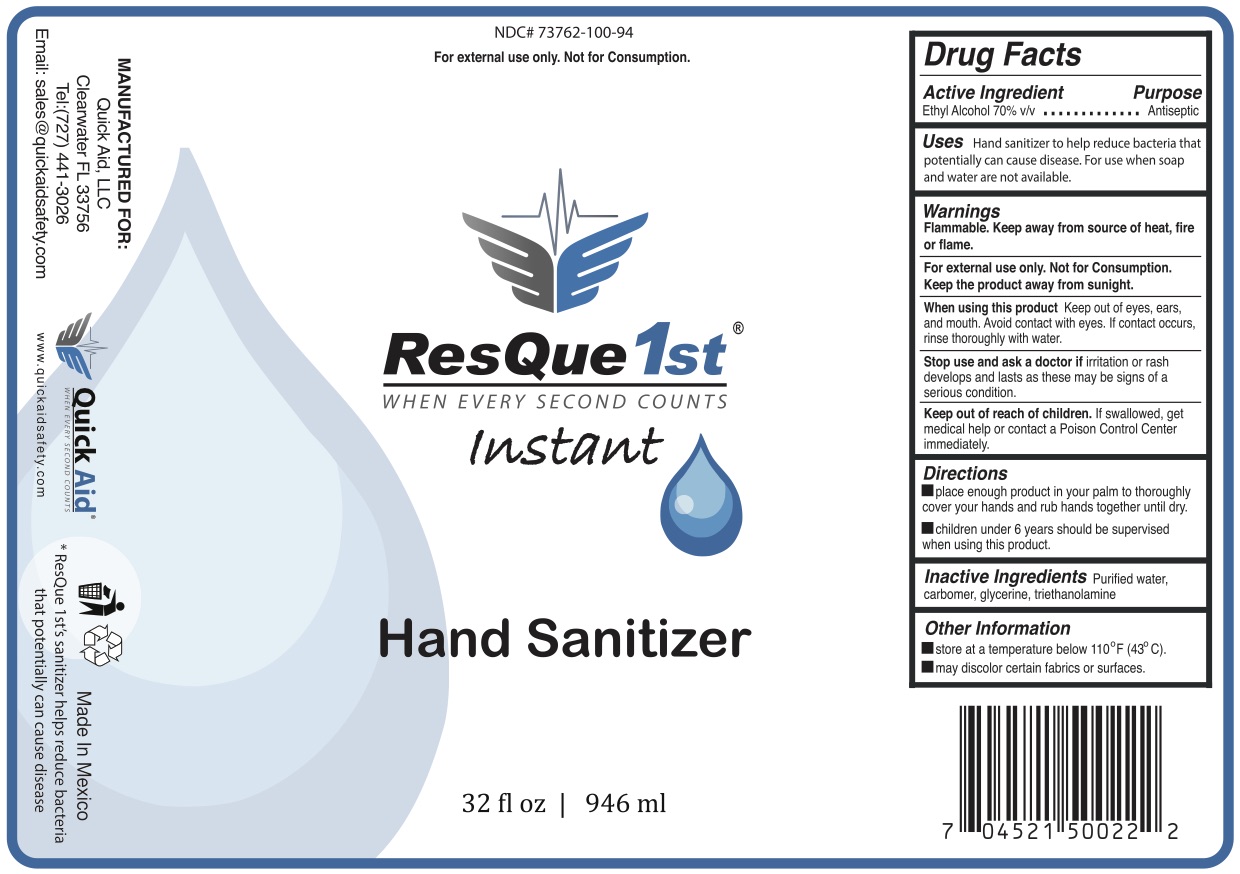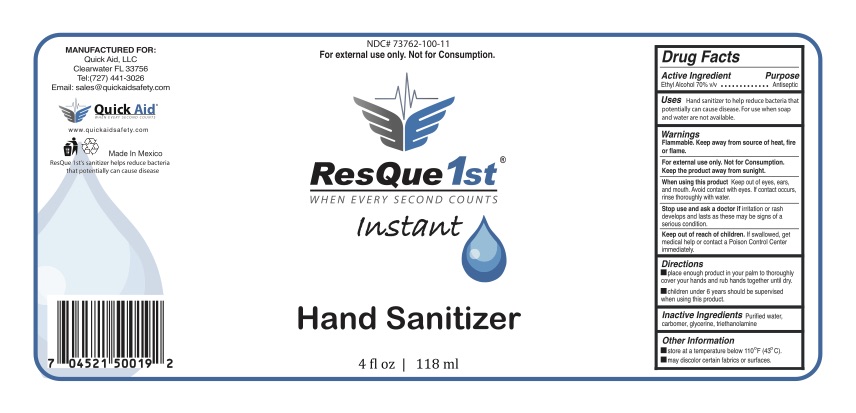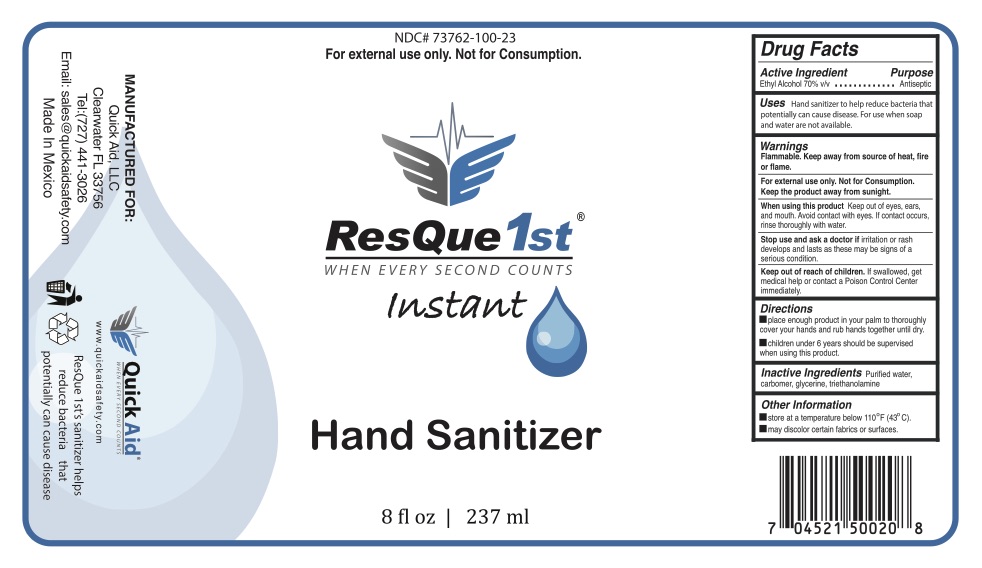 DRUG LABEL: ResQue1st Hand Sanitizer
NDC: 73762-100 | Form: GEL
Manufacturer: RESQUE1ST LLC
Category: otc | Type: HUMAN OTC DRUG LABEL
Date: 20200810

ACTIVE INGREDIENTS: ALCOHOL 70 mL/100 mL
INACTIVE INGREDIENTS: HYDROXYETHYL CELLULOSE, UNSPECIFIED; GLYCERIN; WATER

ResQue1st Instant Hand Sanitizer

ResQue1st Hand Sanitizer Gel

Drug Facts

Active Ingredient(s)

Alcohol 70% v/v.

Purpose

Antiseptic

Use

Hand sanitizer to help reduce bacteria on the skin.

Warnings

Flammable. Keep away from source of heat, fire or flame.

For external use only.

When using this product avoid contact with eyes. If contact occurs, rinse thoroughly with water.

Stop use and ask a doctor if irritation or redness develops and lasts.

Keep out of reach of children. If swallowed, get medical help or contact a Poison Control Center right away.

Directions

- Place enough product in your palm to thoroughly cover your hands and rub hands together until dry.
- Children under 6 years should be supervised when using this product.

Storage

- Store at a temperature below 110°F (43°C)
- May discolor certain fabrics or surfaces

Inactive ingredients

Glycerine, Hydroxyethylcellulose, Purified water USP